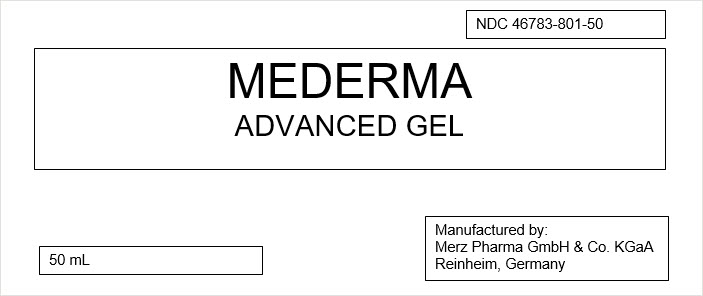 DRUG LABEL: Mederma Advanced
NDC: 46783-801 | Form: GEL
Manufacturer: Merz North America
Category: otc | Type: HUMAN OTC DRUG LABEL
Date: 20240311

ACTIVE INGREDIENTS: ALLANTOIN 5 mg/1 mL
INACTIVE INGREDIENTS: WATER; EGG PHOSPHOLIPIDS; XANTHAN GUM; ALCOHOL; SORBIC ACID; METHYLPARABEN; ONION; PANTHENOL; POLYETHYLENE GLYCOL 200; HYALURONATE SODIUM

Mederma Advanced Gel

PRINCIPAL DISPLAY PANEL - 50 mL Tube Box Label

NDC 46783-801-50

MEDERMA
ADVANCED GEL

50 mL

Manufactured by:
Merz Pharma GmbH & Co. KGaA
Reinheim, Germany